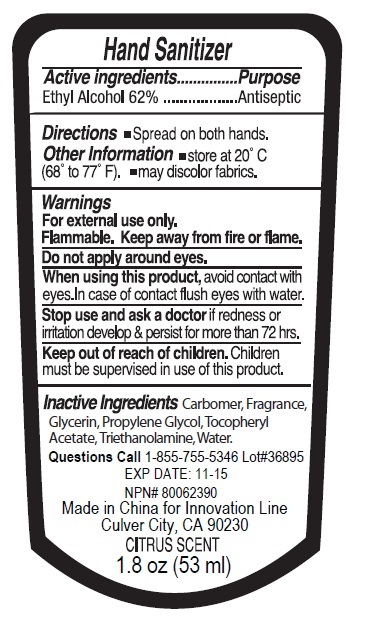 DRUG LABEL: Antiseptic Hand Sanitizer
NDC: 76138-113 | Form: GEL
Manufacturer: Innovation Specialties Inc
Category: otc | Type: HUMAN OTC DRUG LABEL
Date: 20240710

ACTIVE INGREDIENTS: ALCOHOL 62 mL/100 mL
INACTIVE INGREDIENTS: CARBOMER HOMOPOLYMER, UNSPECIFIED TYPE; GLYCERIN; PROPYLENE GLYCOL; .ALPHA.-TOCOPHEROL ACETATE; TROLAMINE; WATER

Antiseptic Hand Sanitizer

Active ingredients

Ethyl Alcohol 62%

Purpose

Antiseptic

Keep out of reach of children.Children must be supervised in use of this product.

Use

To help clean hands

Warnings

For external use only.

Flammable. Keep away from fire or flame.

Do not apply around eyes.

When using this product, avoid contact with eyes. In case of contact flush eyes with water.

Stop use and ask a doctor if redness or irritation develop & persist for more than 72 hrs.

Directions

• Spread on both hands.

Inactive ingredients

Carbomer, Fragrance, Glycerin, Propylene Glycol, Tocopheryl Acetate, Triethanolamine, Water.

Other Information

• store at 20°C (68° to 77° F). • may discolor fabrics.

Questions

Call1-855-755-5346

Made in China for Innovation Line
Culver City, CA 90230
CITRUS SCENT